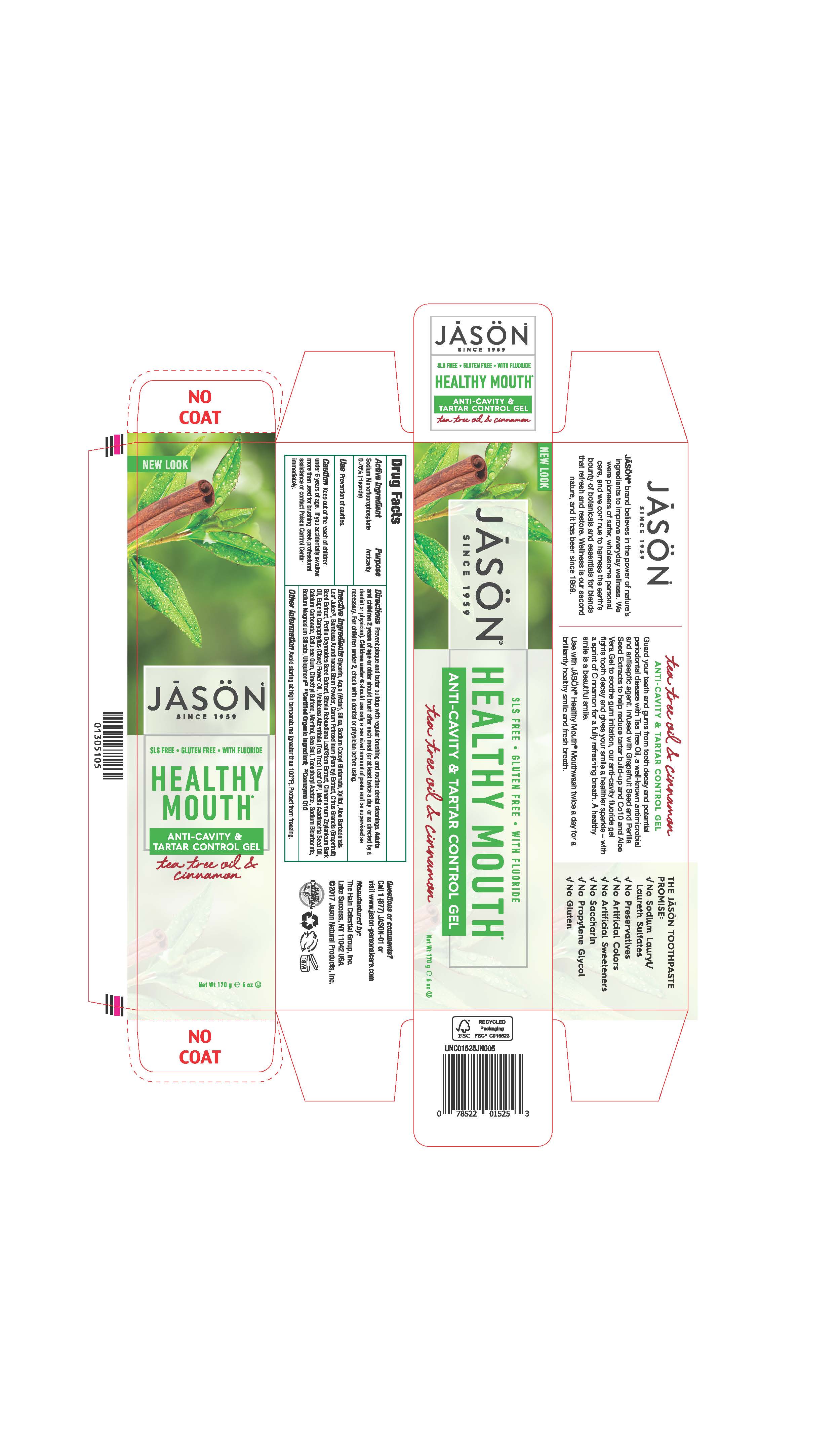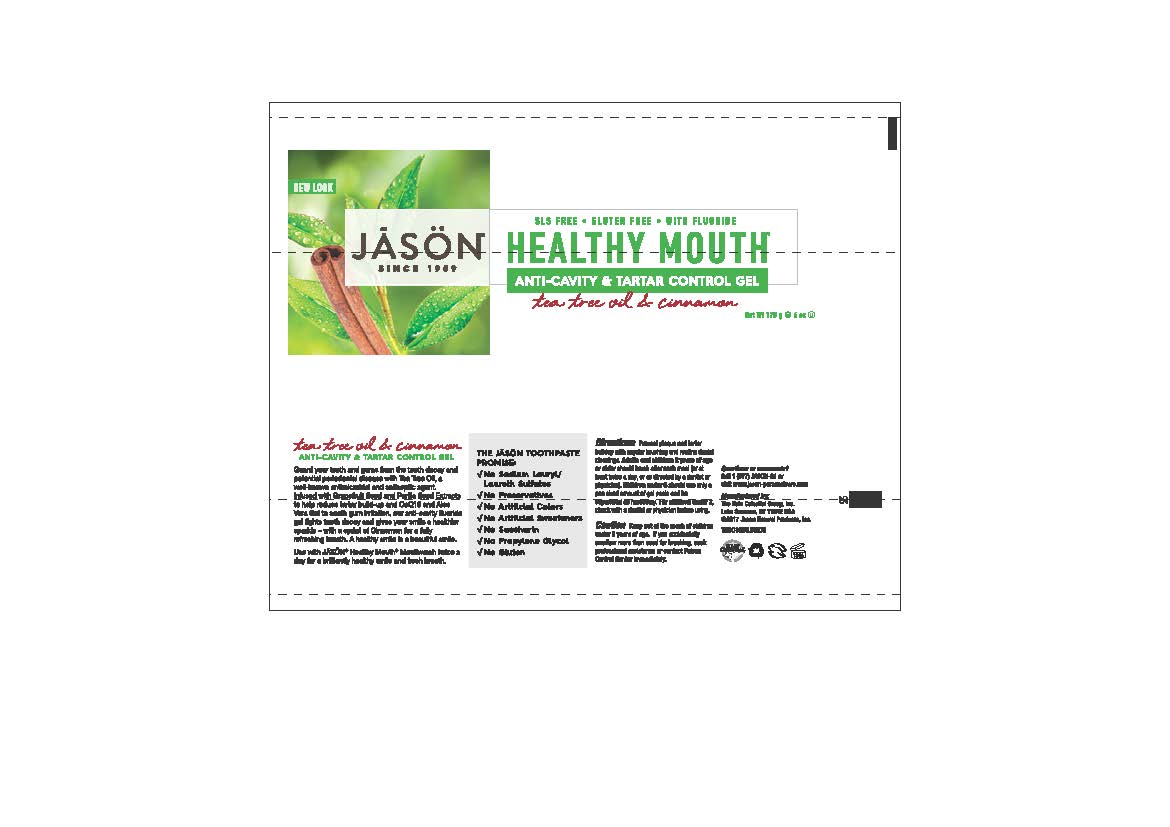 DRUG LABEL: Jason Healthy Mouth Anticavity Tartar Control Tea Tree Cinnamon
NDC: 61995-0525 | Form: GEL
Manufacturer: The Hain Celestial Group, Inc.
Category: otc | Type: HUMAN OTC DRUG LABEL
Date: 20210412

ACTIVE INGREDIENTS: SODIUM MONOFLUOROPHOSPHATE 0.76 g/100 g
INACTIVE INGREDIENTS: TEA TREE OIL; MENTHOL, UNSPECIFIED FORM; CLOVE OIL; AZADIRACHTA INDICA SEED OIL; CINNAMON BARK OIL; GLYCERIN; WATER; SILICON DIOXIDE; SODIUM COCOYL GLUTAMATE; XYLITOL; ALOE VERA LEAF; BAMBUSA ARUNDINACEA STEM; GRAPEFRUIT SEED OIL; PARSLEY; PERILLA FRUTESCENS SEED; STEVIA REBAUDIUNA LEAF; UBIDECARENONE; MAGNESIUM SILICATE; SEA SALT; CALCIUM CARBONATE; CARBOXYMETHYLCELLULOSE SODIUM; DIMETHYL SULFONE; SODIUM BICARBONATE; .ALPHA.-TOCOPHEROL ACETATE; ASCORBIC ACID; ANHYDROUS CITRIC ACID; EUGENOL

Healthy Mouth Toothgel

PURPOSE

Anticavity

WARNINGS

Avoid storing at high temperatures (greater than 100°F). Protect from freezing. If you accidentally swalow more than used for brushing, seek professional assistance or contact Poison Control immediately.

Keep out of reach of children under 6 years of age.If you accidentally swallow more than used for brushing, get medical help or contact Poison Control Center immediately.

DOSAGE AND ADMINISTRATION

Prevent plaque and tartar buildup with regular drushing. Adults and children 2 years of age or older should brush teeth after each meal (or at least twice a day, or as directed by a dentist or physician). Children under 6: Should use only a pea sized amount of paste and be supervised as necessary. Children under 2, check with a dentist or physician before using.

INACTIVE INGREDIENT

Glycerin, Aqua (Water), Hydrated Silica, Sodium Cocoyl Glutamate, Xylitol, Cinnamomum Zeylanicum (Cinnamon) Leaf Oil, Eugenia Caryophyllus (Clove) Flower Oil, Melaleuca Alternifolia (Tea Tree) Leaf Oil (1), Melia Azadirachta Seed Oil, Aloe Barbadensis Leaf Juice (1), Bambusa Arundinacea Stem Powder, Carum Petroselinum (Parsley) Extract, Citrus Grandis (Grapefruit) Seed Extract, Perilla Ocymoides Seed Extract, Stevia Rebaudiana Leaf/Stem Extract, Ascorbic Acid, Tocopheryl Acetate, Calcium Carbonate, Cellulose Gum, Citric Acid, Menthol, Sea Salt, Sodium Bicarbonate, Sodium Magnesium Silicate, Ubiquinone, Eugenol

(1) Certified Organic Ingredients

(2) Coenzyme Q10

INDICATIONS AND USAGE

Use: Prevention of cavities

ACTIVE INGREDIENT

Sodium Monofluorophosphate 0.76%